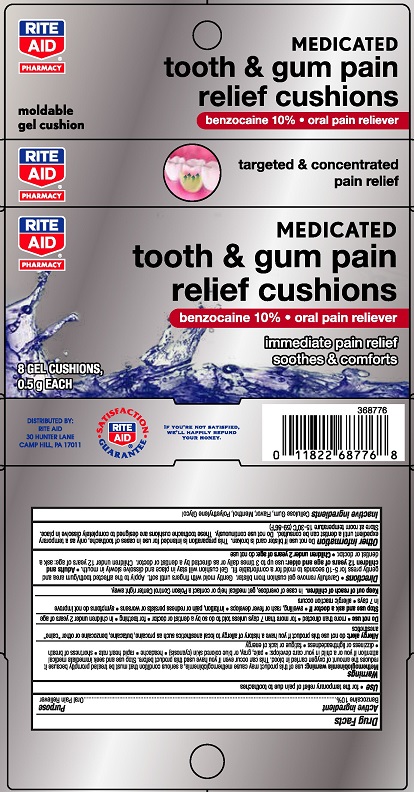 DRUG LABEL: Rite Aid Tooth and Gum Pain Relief

NDC: 11822-6035 | Form: STRIP
Manufacturer: Rite Aid
Category: otc | Type: HUMAN OTC DRUG LABEL
Date: 20230111

ACTIVE INGREDIENTS: BENZOCAINE 10 g/100 g
INACTIVE INGREDIENTS: POLYETHYLENE GLYCOL, UNSPECIFIED; CARBOXYMETHYLCELLULOSE SODIUM, UNSPECIFIED FORM; MENTHOL

Rite Aid Tooth & Gum Pain Relief Cushions

Drug Facts

Active ingredient

Benzocaine 10%

Purpose

Oral Pain Reliever

Use

- for the temporary relief of pain due to toothaches

Warnings

Methemoglobinemia warning: use of this product may cause methemoglobinemia, a serious condition that must be treated promptly because it reduces the amount of oxygen carried in blood. This can occur even if you have used this product before. Stop use and seek immediate medical attention if you or a child in your care develops:

- pale, gray, or blue colored skin (cyanosis)
- headache
- rapid heart rate
- shortness of breath
- dizziness or lightheadedness
- fatigue or lack of energy

Allergy alert: do not use this product if you have a history of allergy to local anesthetics such as procaine, butacaine, benzocaine or other “caine” anesthetics

Do not use

- more than directed
- for more than 7 days unless told to do so by a dentist or doctor
- for teething
- in children under 2 years of age

Stop use and ask a doctor if

- swelling, rash or fever develops
- irritation, pain or redness persists or worsens
- symptoms do not improve in 7 days
- allergic reaction occurs

Keep out of reach of children. In case of overdose, get medical help or contact a Poison Control Center right away.

Directions

- Carefully remove gel cushion from blister. Gently mold iwth fingers until soft. Apply to affected tooth/gum area and gently press for 5-10 seconds to mold for a comfortable fit. Gel cushion will stay in place and dissolve slowly in mouth.
- Adults and children 12 years of age and older: use up to 3 times daily or as directed by dentist or doctor.
- Children under 12 years of age: ask a dentist or doctor
- Children under 2 years of age: do not use

Other information

Do not use if blister card is broken. This preparation is intended for use in cases of toothache, only as a temporary expedient until a dentist can be consulted. Do not use continuously. These toothache cushions are designed to completely dissolve in place.

Store at room temperature 15-30°C (59-86°F)

Inactive ingredients

Cellulose Gum, Flavor, Menthol, Polyethylene Glycol

DISTRIBUTED BY:

RITE AID

30 HUNTER LANE

CAMP HILL, PA 17011

PACKAGE LABEL

RITE AID® PHARMACY

MEDICATED

tooth & gum pain relief cushions

benzocaine 10% • oral pain reliever

immediate pain relief

soothes & comforts

8 GEL CUSHIONS, 0.5 g EACH